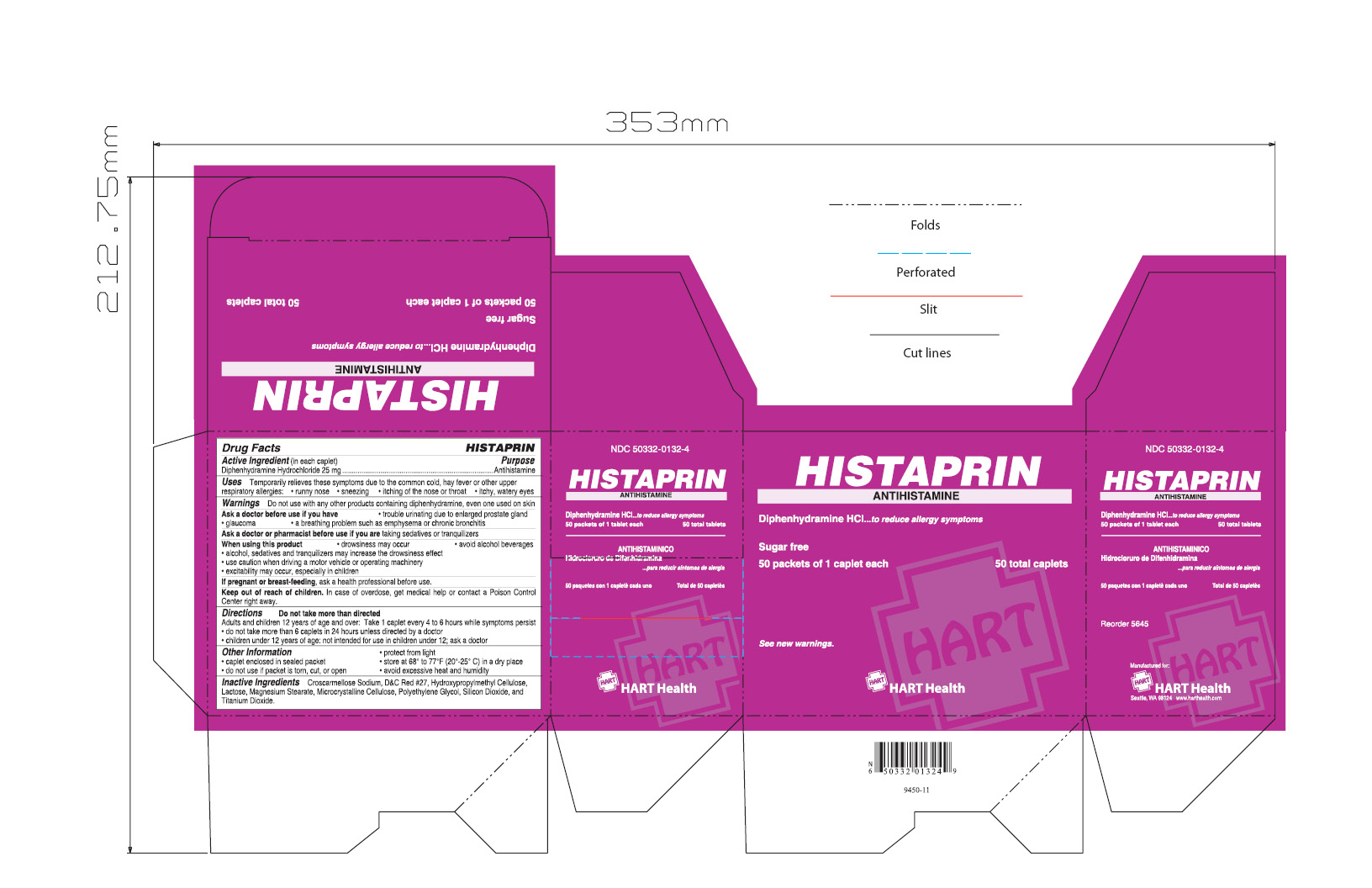 DRUG LABEL: HISTAPRIN
NDC: 50332-0132 | Form: TABLET
Manufacturer: NorMed
Category: otc | Type: HUMAN OTC DRUG LABEL
Date: 20120711

ACTIVE INGREDIENTS: DIPHENHYDRAMINE HYDROCHLORIDE 25 mg/1 1
INACTIVE INGREDIENTS: CROSCARMELLOSE SODIUM; LACTOSE; MAGNESIUM STEARATE; CELLULOSE, MICROCRYSTALLINE; SILICON DIOXIDE; TITANIUM DIOXIDE

HISTAPRIN

Active Ingredient (in each caplet)

Diphenhydramine Hydrochloride 25mg

PURPOSE

Antihistamine

INDICATIONS AND USAGE

Temporarily relieves these symptoms due to the common cold, hay fever, or other upper respiratory allergies:

- runny nose
- sneezing
- itching of the nose or throat
- itchy, watery eyes

Do not use with any other products containing diphenhydramine, even one used on skin

Ask a doctor before use if you have

- trouble urinating due to enlarged prostate gland
- glaucoma
- a breathing problem such as emphysema or chronic bronchiti

Ask a doctor or pharmacist before use if you are taking sedatives or tranquilizers

When using the product

- drowsiness may occur
- avoid alcoholic beverages
- alcohol, sedatives and tranquilizers may increase the drowsiness effect
- use caution when driving a motor vehicle or operating machinery
- excitability may occur, especially in children

PREGNANCY OR BREAST FEEDING

If pregnant or breast-feeding, ask a health professional before use.

Keep out of reach of children. In case of overdose, get medical help or contact a Poison Control Center right away.

Directions

Do not take more than directed

Adults and children 12 years of age and over:

- Take 1 caplet every 4 to 6 hours while symptoms persist

- do not take more than 6 caplets in 24 hours unless directed by a doctor

Children under 12 years of age: not intended for use in children under 12; ask a doctor

INACTIVE INGREDIENT

Enter section text here